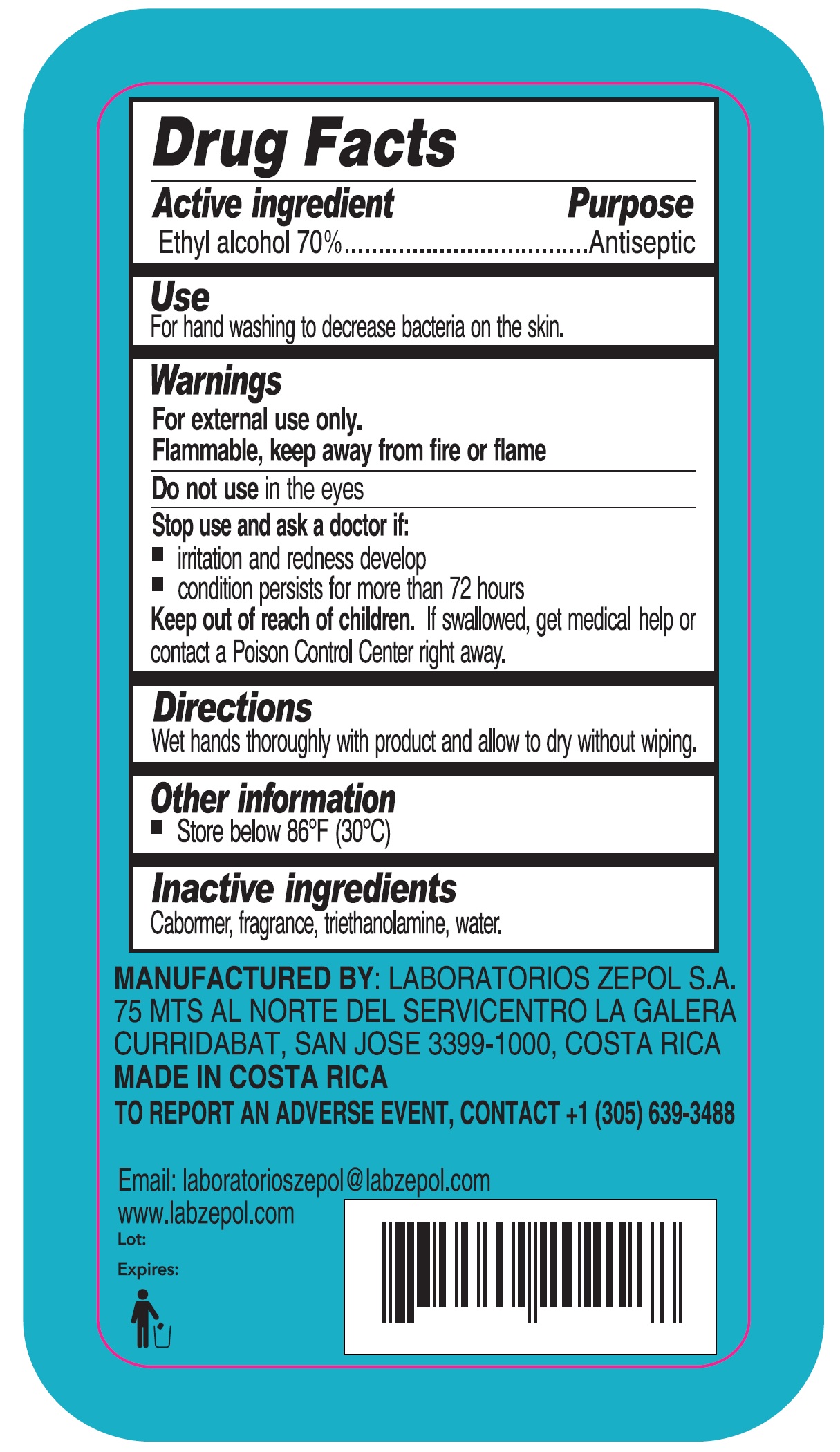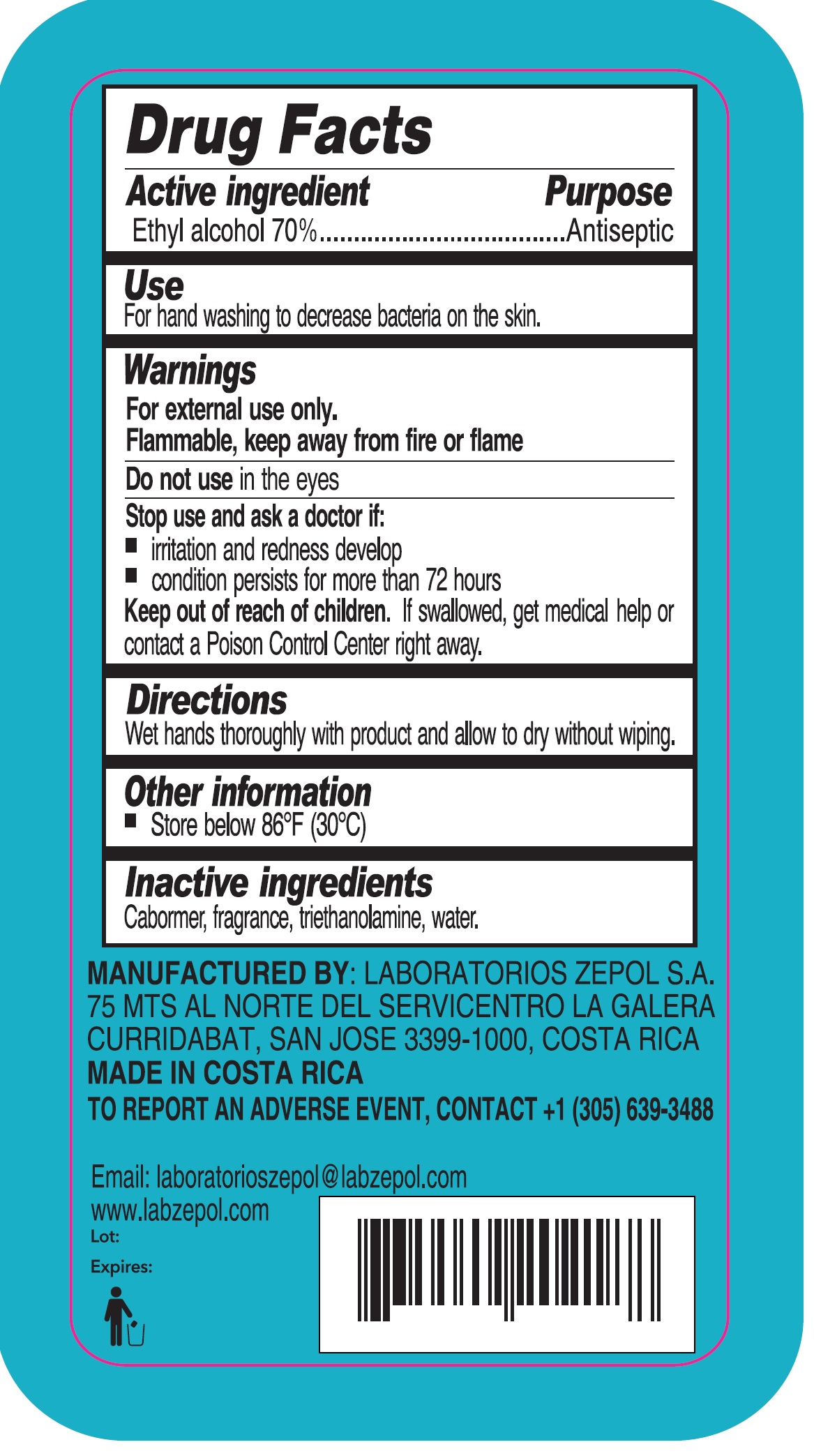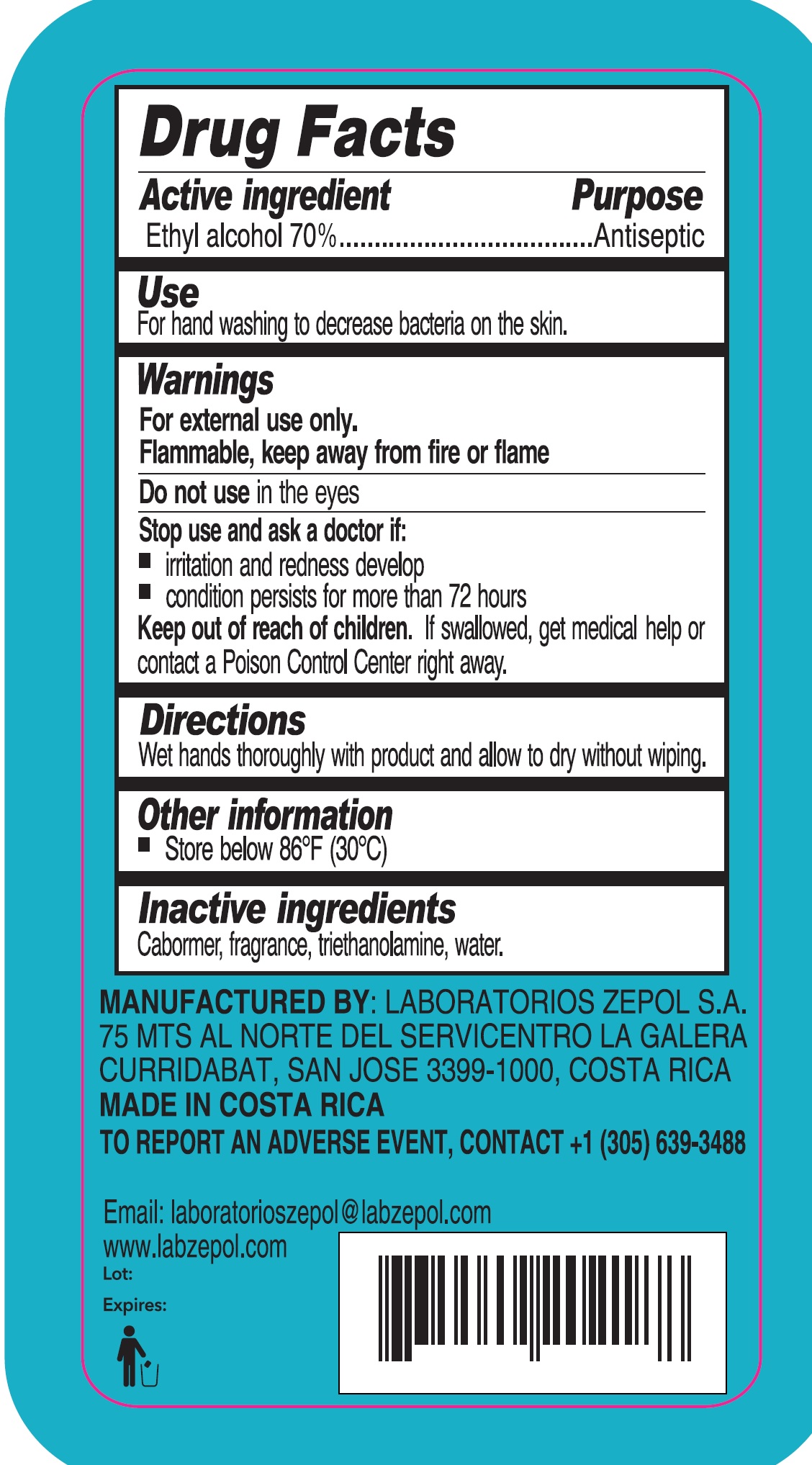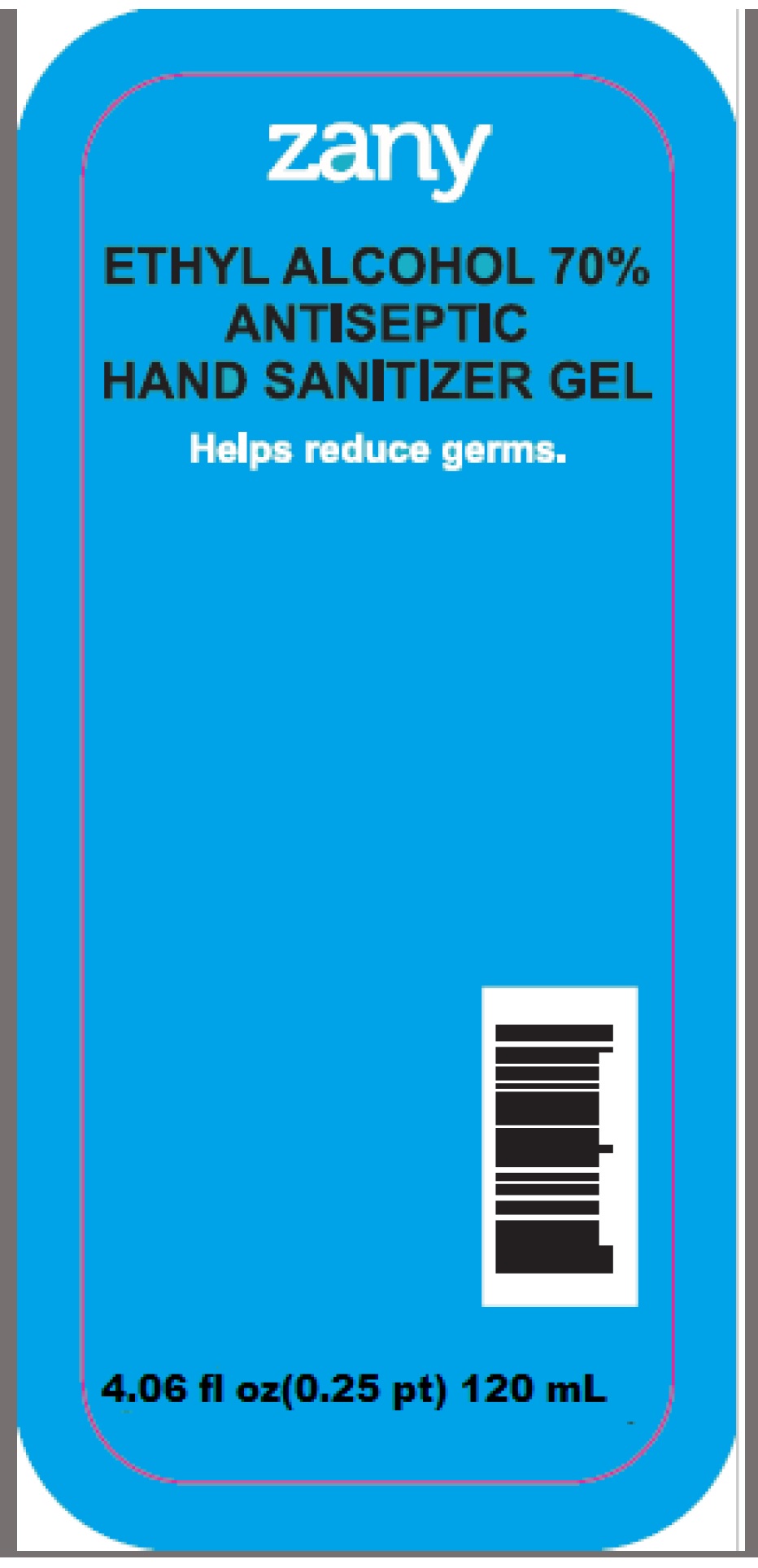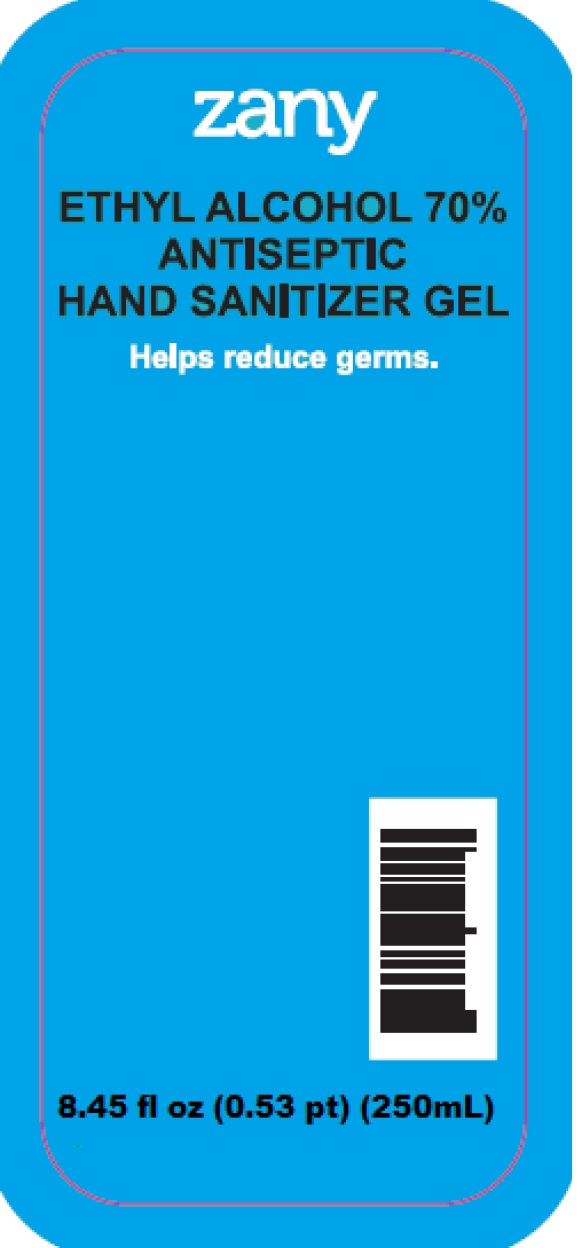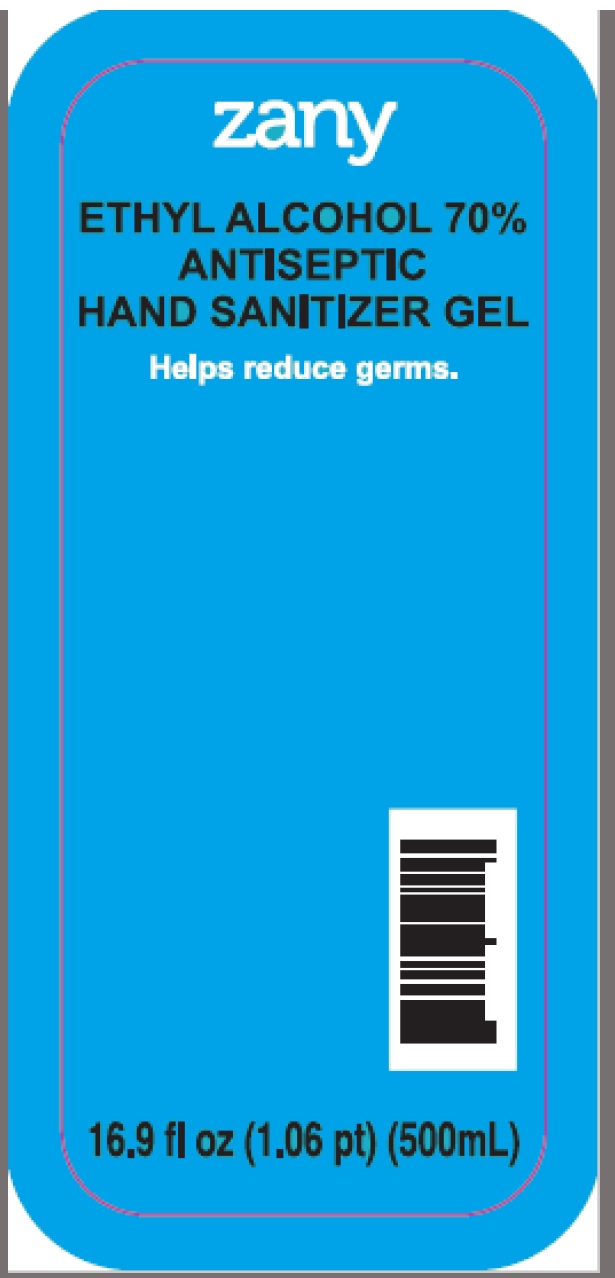 DRUG LABEL: Zany Antiseptic Gel
NDC: 55715-004 | Form: GEL
Manufacturer: Laboratorios Zepol S.A.
Category: otc | Type: HUMAN OTC DRUG LABEL
Date: 20231201

ACTIVE INGREDIENTS: ALCOHOL 0.7 mL/1 mL
INACTIVE INGREDIENTS: CARBOMER HOMOPOLYMER, UNSPECIFIED TYPE; TROLAMINE; WATER

Zany Antiseptic Gel

Active ingredient

Ethyl alcohol 70%

Purpose

Antiseptic

Use

For hand washing to decrease bacteria on the skin.

Warnings

For external use only.

Flammable, keep away from fire or flame.

Do not use

in the eyes

Stop use and ask a doctor if:

- irritation and redness develop
- condition persists for more than 72 hours

Keep out of reach of children.

If swallowed, get medical help or contact a Poison Control Center right away.

Directions

Wet hands thoroughly with product and allow to dry without wiping.

Other information

- Store below 86°F (30°C)

Inactive ingredients

Carbomer, fragrance, triethanolamine, water.